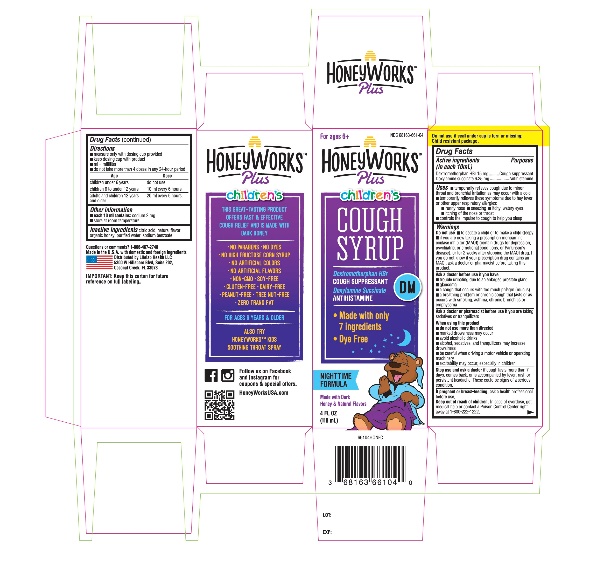 DRUG LABEL: Childrens HoneyWorks Plus Nighttime Cough Syrup
NDC: 68163-661 | Form: SOLUTION
Manufacturer: RARITAN PHARMACEUTICALS INC
Category: otc | Type: HUMAN OTC DRUG LABEL
Date: 20251014

ACTIVE INGREDIENTS: DEXTROMETHORPHAN HYDROBROMIDE 15 mg/10 mL; DOXYLAMINE SUCCINATE 6.25 mg/10 mL
INACTIVE INGREDIENTS: ANHYDROUS CITRIC ACID; HONEY; WATER; SODIUM BENZOATE

HoneyWorks Children’s Cough Syrup Drug facts

ACTIVE INGREDIENT

PURPOSE

Active ingredients (in each 10 ml) | Purposes
Dextromethorphan HBr, USP 15 mg | Cough suppressant
Doxylamine Succinate, USP 6.25 mg | Antihistamine

- Uses
- temporarily relieves cough due to minor throat and bronchial irritation as may occur with a cold
- temporarily relieves these symptoms due to hay fever or other upper respiratory allergies:
  - runny nose
  - sneezing
  - itchy, watery eyes
  - itching of the nose or throat
- controls the impulse to cough to help you sleep

Warnings

Do not use

- to sedate a child or to make a child sleepy
- if you are now taking a prescription monoamine oxidase inhibitor (MAOI) (certain drugs for depression, psychiatric, or emotional conditions, or Parkinson's disease), or for 2 weeks after stopping the MAOI drug. If you do not know if your prescription drug contains an MAOI, ask a doctor or pharmacist before taking this product.

Ask a doctor before use if you have

- trouble urinating due to an enlarged prostate gland
- glaucoma
- a cough that occurs with too much phlegm (mucus)
- a breathing problem or chronic cough that lasts or as occurs with smoking, asthma, chronic bronchitis or emphysema

Ask a doctor or pharmacist before use if you aretaking sedatives or tranquilizers

When using this product

- do not use more than directed
- marked drowsiness may occur
- avoid alcoholic drinks
- alcohol, sedatives, and tranquilizers may increase drowsiness
- be careful when driving a motor vehicle or operating machinery
- excitability may occur, especially in children

Stop use and ask a doctor ifcough lasts more than 7 days, comes back, or is accompanied by fever, rash, or persistent headache. These could be signs of a serious condition.

PREGNANCY OR BREAST FEEDING

If pregnant or breast-feeding,ask a health professional before use.

Keep out of reach of children.In case of overdose, get medical help or contact a Poison Control Center right away.

Directions

- measure only with dosing cup provided
- keep dosing cup with product
- ml = milliliter
- do not take more than 4 doses in any 24-hour period

age | dose
children under 6 years | do not use
children 6 to under 12 years | 10 ml every 6 hours
adults and children 12 years and older | 20 ml every 6 hours

Other information

- each 10 ml contains: sodium 2 mg
- store at room temperature

Inactive ingredients

citric acid, natural flavor, organic honey, purified water, sodium benzoate,

Questions or comments?

1-866-467-2748

Made in the U.S.A. with domestic and foreign ingredients

Distributed by Lifelab Health LLC

5300 W Hillsboro Blvd, Suite 202,

Coconut Creek, FL 33073

PRINCIPAL DISPLAY PANEL - 118 ml Bottle Carton

NDC 68163-661-04

HONEYWORKS™ Plus

Children’s

COUGH SYRUP

Dextromethorphan HBr
(COUGH SUPPRESSANT)
Doxylamine Succinate (ANTIHISTAMINE)

NIGHTTIME FORMULA

GRAPE FLAVOR

THIS GREAT-TASTING PRODUCT OFFERS FAST & EFFECTIVE COUGH RELIEF NAD IS MADE WITH ORGANIC DARK HONEY

- NO PARABENS
- NO DYES
- NO HIGH FRUCTOSE CORN SYRUP
- NO ARTIFICIAL FLAVORS
- NON-GMO
- SOY-FREE
- GLUTEN FREE
- DAIRY-FREE
- PEANUT-FREE
- TREE NUT-FREE
- ZERO TRANS FAT

FOR AGES 6 YEARS & OLDER

ALSO TRY HONEYWORKS™ KIDS SOOTHING THROAT SPRAY

4 FL OZ (118 mL)

IMPORTANT: Keep this carton for future reference on full labeling.